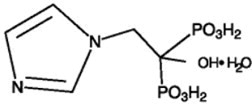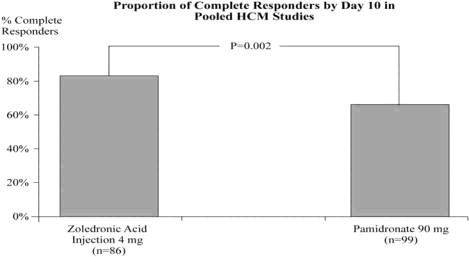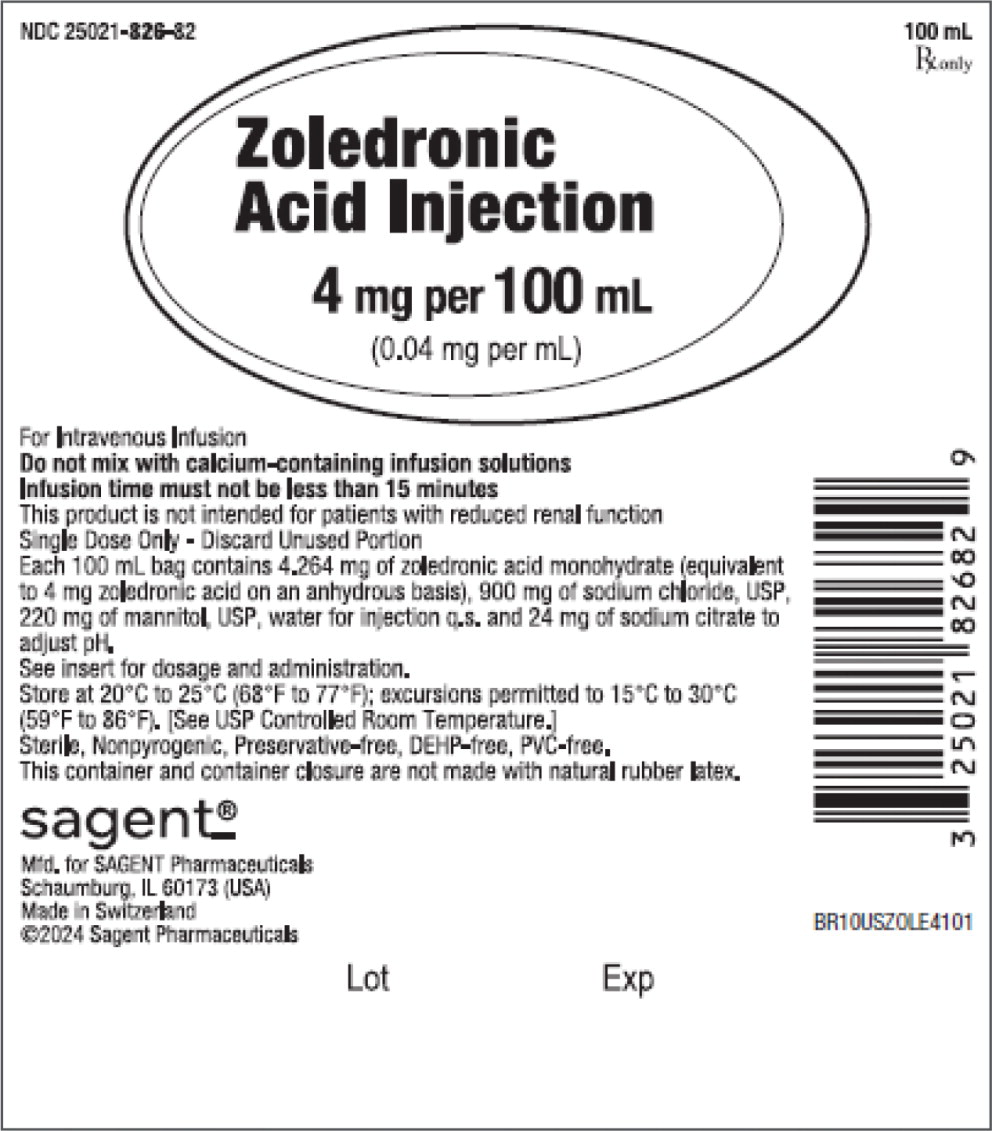 DRUG LABEL: zoledronic acid
NDC: 25021-826 | Form: INJECTION, SOLUTION
Manufacturer: Sagent Pharmaceuticals
Category: prescription | Type: HUMAN PRESCRIPTION DRUG LABEL
Date: 20250311

ACTIVE INGREDIENTS: zoledronic acid 0.04 mg/1 mL
INACTIVE INGREDIENTS: sodium chloride; mannitol; water; sodium citrate

HIGHLIGHTS OF PRESCRIBING INFORMATION

These highlights do not include all the information needed to use ZOLEDRONIC ACID INJECTION safely and effectively. See full prescribing information for ZOLEDRONIC ACID INJECTION.
ZOLEDRONIC ACID INJECTION, for intravenous use
Initial U.S. Approval: 2001

1 INDICATIONS AND USAGE

Zoledronic Acid Injection is a bisphosphonate indicated for the treatment of:

- Hypercalcemia of malignancy. (1.1)
- Patients with multiple myeloma and patients with documented bone metastases from solid tumors, in conjunction with standard antineoplastic therapy. Prostate cancer should have progressed after treatment with at least one hormonal therapy. (1.2)

Limitations of Use: The safety and efficacy of Zoledronic Acid Injection has not been established for use in hyperparathyroidism or non-tumor-related hypercalcemia.

2 DOSAGE AND ADMINISTRATION

Hypercalcemia of malignancy (2.1)

- 4 mg as a single-dose intravenous infusion over no less than 15 minutes. (2.1)
- 4 mg as retreatment after a minimum of 7 days. (2.1)

Multiple myeloma and bone metastasis from solid tumors. (2.2)

- 4 mg as a single-dose intravenous infusion over no less than 15 minutes every 3 to 4 weeks for patients with creatinine clearance of greater than 60 mL/min. (2.2)
- This premixed ready-to-use bag is intended only for patients with normal renal function (creatinine clearance greater than 60 mL/min.) (2.2)
- Coadminister oral calcium supplements of 500 mg and a multiple vitamin containing 400 international units of vitamin D daily. (2.2)

Administer through a separate infusion line and do not allow to come in contact with any calcium or divalent cation-containing solutions. (2.3)

3 DOSAGE FORMS AND STRENGTHS

Zoledronic Acid Injection: 4 mg in a 100 mL (0.04 mg per mL) single-dose bag (3)

4 CONTRAINDICATIONS

Hypersensitivity to any component of Zoledronic Acid Injection (4)

5 WARNINGS AND PRECAUTIONS

- Patients being treated with Zoledronic Acid Injection should not be treated with Reclast®. (5.1)
- Adequately rehydrate patients with hypercalcemia of malignancy prior to administration of Zoledronic Acid Injection and monitor electrolytes during treatment. (5.2)
- Renal toxicity may be greater in patients with renal impairment. Do not use doses greater than 4 mg. Treatment in patients with severe renal impairment is not recommended. Monitor serum creatinine before each dose. (5.3)
- Osteonecrosis of the jaw (ONJ) has been reported. Preventive dental exams should be performed before starting Zoledronic Acid Injection. Avoid invasive dental procedures. (5.4)
- Severe incapacitating bone, joint, and/or muscle pain may occur. Discontinue Zoledronic Acid Injection if severe symptoms occur. (5.5)
- Atypical subtrochanteric and diaphyseal femoral fractures have been reported in patients receiving bisphosphonate therapy. These fractures may occur after minimal or no trauma. Evaluate patients with thigh or groin pain to rule out a femoral fracture. Consider drug discontinuation in patients suspected to have an atypical femur fracture. (5.6)
- Hypocalcemia: Correct before initiating Zoledronic Acid Injection. Adequately supplement patients with calcium and vitamin D. Monitor serum calcium closely with concomitant administration of other drugs known to cause hypocalcemia to avoid severe or life-threatening hypocalcemia. (5.9)
- Zoledronic Acid Injection can cause fetal harm. Advise females of reproductive potential of potential risk to a fetus and to use effective contraception. (5.10, 8.1, 8.3)

6 ADVERSE REACTIONS

The most common adverse reactions (greater than 25%) were nausea, fatigue, anemia, bone pain, constipation, fever, vomiting, and dyspnea. (6.1)

To report SUSPECTED ADVERSE REACTIONS, contact Sagent Pharmaceuticals at 1-866-625-1618 or FDA at 1-800-FDA-1088 or www.fda.gov/medwatch.

7 DRUG INTERACTIONS

- Aminoglycosides: May have an additive effect to lower serum calcium for prolonged periods. (7.1)
- Loop Diuretics: Concomitant use with Zoledronic Acid Injection may increase risk of hypocalcemia. (7.2)
- Nephrotoxic Drugs: Use with caution. (7.3)

8 USE IN SPECIFIC POPULATIONS

- Lactation: Advise not to breastfeed. (8.2)
- Females and Males of Reproductive Potential: Verify pregnancy status prior to initiation of Zoledronic Acid Injection. May impair fertility. Counsel patients on pregnancy planning and prevention. (8.3)
- Pediatric Use: Not indicated for use in pediatric patients. (8.4)
- Geriatric Use: Special care to monitor renal function. (8.5)

FULL PRESCRIBING INFORMATION

1 INDICATIONS AND USAGE

1.1 Hypercalcemia of Malignancy

Zoledronic Acid Injection is indicated for the treatment of hypercalcemia of malignancy defined as an albumin-corrected calcium (cCa) of greater than or equal to 12 mg/dL [3 mmol/L] using the formula: cCa in mg/dL = Ca in mg/dL + 0.8 (4 g/dL – patient albumin [1g/dL]).

1.2 Multiple Myeloma and Bone Metastases of Solid Tumors

Zoledronic Acid Injection is indicated for the treatment of patients with multiple myeloma and patients with documented bone metastases from solid tumors, in conjunction with standard antineoplastic therapy. Prostate cancer should have progressed after treatment with at least one hormonal therapy.

Limitations of Use

The safety and efficacy of Zoledronic Acid Injection in the treatment of hypercalcemia associated with hyperparathyroidism or with other non-tumor-related conditions have not been established.

2 DOSAGE AND ADMINISTRATION

Parenteral drug products should be inspected visually for particulate matter and discoloration prior to administration, whenever solution and container permit.

2.1 Hypercalcemia of Malignancy

The maximum recommended dose of Zoledronic Acid Injection in hypercalcemia of malignancy (albumin-corrected serum calcium greater than or equal to 12 mg/dL [3 mmol/L]) is 4 mg. The 4 mg dose must be given as a single-dose intravenous infusion over no less than 15 minutes. Patients who receive Zoledronic Acid Injection should have serum creatinine assessed prior to each treatment.

Dose adjustments of Zoledronic Acid Injection are not necessary in treating patients for hypercalcemia of malignancy presenting with mild-to-moderate renal impairment prior to initiation of therapy (serum creatinine less than 400 μmol/L or less than 4.5 mg/dL).

Patients should be adequately rehydrated prior to administration of Zoledronic Acid Injection [see Warnings and Precautions (5.2)].

Consideration should be given to the severity of, as well as the symptoms of, tumor-induced hypercalcemia when considering use of Zoledronic Acid Injection. Vigorous saline hydration, an integral part of hypercalcemia therapy, should be initiated promptly and an attempt should be made to restore the urine output to about 2 L/day throughout treatment. Mild or asymptomatic hypercalcemia may be treated with conservative measures (i.e., saline hydration, with or without loop diuretics). Patients should be hydrated adequately throughout the treatment, but overhydration, especially in those patients who have cardiac failure, must be avoided. Diuretic therapy should not be employed prior to correction of hypovolemia.

Retreatment with Zoledronic Acid Injection 4 mg may be considered if serum calcium does not return to normal or remain normal after initial treatment. It is recommended that a minimum of 7 days elapse before retreatment, to allow for full response to the initial dose. Renal function must be carefully monitored in all patients receiving Zoledronic Acid Injection and serum creatinine must be assessed prior to retreatment with Zoledronic Acid Injection [see Warnings and Precautions (5.2)].

2.2 Multiple Myeloma and Bone Metastases of Solid Tumors

The recommended dose of Zoledronic Acid Injection in patients with multiple myeloma and metastatic bone lesions from solid tumors for patients with creatinine clearance (CrCl) greater than 60 mL/min is 4 mg infused over no less than 15 minutes every 3 to 4 weeks. The optimal duration of therapy is not known.

This product is not intended for use with patients with reduced renal function (CrCl 60 mL/min or less).

During treatment, serum creatinine should be measured before each Zoledronic Acid Injection dose and treatment should be withheld for renal deterioration. In the clinical studies, renal deterioration was defined as follows:

For patients with normal baseline creatinine, increase of 0.5 mg/dL
For patients with abnormal baseline creatinine, increase of 1 mg/dL

In the clinical studies, Zoledronic Acid Injection treatment was resumed only when the creatinine returned to within 10% of the baseline value. Zoledronic Acid Injection should be reinitiated at the same dose as that prior to treatment interruption.

Patients should also be administered an oral calcium supplement of 500 mg and a multiple vitamin containing 400 international units of vitamin D daily.

2.3 Preparation of Solution

Zoledronic Acid Injection must not be mixed with calcium or other divalent cation-containing infusion solutions, such as Lactated Ringer's solution, and should be administered as a single intravenous solution in a line separate from all other drugs.

4 mg per 100 mL Single-Dose Ready-to-Use Bag

Bags of Zoledronic Acid Injection ready-to-use solution for infusion contain overfill allowing for the administration of 100 mL of solution (equivalent to 4 mg zoledronic acid). This solution is ready to use and may be administered directly to the patient without further preparation. For single-dose only.

Caution: After removing the overwrap check for minute leaks by squeezing the inner bag firmly. If leaks are found, discard container as sterility may be compromised. Use only if solution is clear and the container is undamaged.

Preparation for Administration:

1. Close flow control clamp of administration set.
2. Remove cover from port at bottom of container.
3. Insert piercing pin of administration set into port with a twisting motion until the pin is firmly seated. NOTE: See full directions on administration set carton.
4. Suspend container from hanger.
5. Squeeze and release drip chamber to establish proper fluid level in chamber during infusion of Zoledronic Acid Injection.
6. Open flow control clamp to expel air from set. Close clamp.
7. Regulate rate of administration with flow control clamp.

2.4 Method of Administration

Due to the risk of clinically significant deterioration in renal function, which may progress to renal failure, single doses of Zoledronic Acid Injection should not exceed 4 mg and the duration of infusion should be no less than 15 minutes [see Warnings and Precautions (5.3)]. In the trials and in postmarketing experience, renal deterioration, progression to renal failure and dialysis, have occurred in patients, including those treated with the approved dose of 4 mg infused over 15 minutes. There have been instances of this occurring after the initial Zoledronic Acid Injection dose.

3 DOSAGE FORMS AND STRENGTHS

Zoledronic Acid Injection: 4 mg in a 100 mL (0.04 mg per mL) single-dose bag

4 CONTRAINDICATIONS

Hypersensitivity reactions including cases of urticaria and angioedema, and cases of anaphylactic reaction/shock have been reported [see Adverse Reactions (6.2)].

5 WARNINGS AND PRECAUTIONS

5.1 Drugs with Same Active Ingredient or in the Same Drug Class

Zoledronic Acid Injection contains the same active ingredient as found in Reclast® (zoledronic acid). Patients being treated with Zoledronic Acid Injection should not be treated with Reclast or other bisphosphonates.

5.2 Hydration and Electrolyte Monitoring

Patients with hypercalcemia of malignancy must be adequately rehydrated prior to administration of Zoledronic Acid Injection. Loop diuretics should not be used until the patient is adequately rehydrated and should be used with caution in combination with Zoledronic Acid Injection in order to avoid hypocalcemia. Zoledronic Acid Injection should be used with caution with other nephrotoxic drugs.

Standard hypercalcemia-related metabolic parameters, such as serum levels of calcium, phosphate, and magnesium, as well as serum creatinine, should be carefully monitored following initiation of therapy with Zoledronic Acid Injection. If hypocalcemia, hypophosphatemia, or hypomagnesemia occur, short-term supplemental therapy may be necessary.

5.3 Renal Impairment

Zoledronic Acid Injection is excreted intact primarily via the kidney, and the risk of adverse reactions, in particular renal adverse reactions, may be greater in patients with impaired renal function. Safety and pharmacokinetic data are limited in patients with severe renal impairment and the risk of renal deterioration is increased [see Adverse Reactions (6.1)]. Preexisting renal insufficiency and multiple cycles of Zoledronic Acid Injection and other bisphosphonates are risk factors for subsequent renal deterioration with Zoledronic Acid Injection. Factors predisposing to renal deterioration, such as dehydration or the use of other nephrotoxic drugs, should be identified and managed, if possible.

Zoledronic Acid Injection treatment in patients with hypercalcemia of malignancy with severe renal impairment should be considered only after evaluating the risks and benefits of treatment [see Dosage and Administration (2.1)]. In the clinical studies, patients with serum creatinine greater than 400 μmol/L or greater than 4.5 mg/dL were excluded.

Zoledronic Acid Injection treatment is not recommended in patients with bone metastases with severe renal impairment. In the clinical studies, patients with serum creatinine greater than 265 μmol/L or greater than 3.0 mg/dL were excluded and there were only 8 of 564 patients treated with Zoledronic Acid Injection 4 mg by 15-minute infusion with a baseline creatinine greater than 2 mg/dL. Limited pharmacokinetic data exists in patients with creatinine clearance less than 30 mL/min [see Clinical Pharmacology (12.3)].

5.4 Osteonecrosis of the Jaw

Osteonecrosis of the jaw (ONJ) has been reported predominantly in cancer patients treated with intravenous bisphosphonates, including Zoledronic Acid Injection. Many of these patients were also receiving chemotherapy and corticosteroids which may be risk factors for ONJ. The risk of ONJ may increase with duration of exposure to bisphosphonates.

Postmarketing experience and the literature suggest a greater frequency of reports of ONJ based on tumor type (advanced breast cancer, multiple myeloma), and dental status (dental extraction, periodontal disease, local trauma including poorly fitting dentures). Many reports of ONJ involved patients with signs of local infection including osteomyelitis.

Cancer patients should maintain good oral hygiene and should have a dental examination with preventive dentistry prior to treatment with bisphosphonates.

While on treatment, these patients should avoid invasive dental procedures if possible. For patients who develop ONJ while on bisphosphonate therapy, dental surgery may exacerbate the condition. For patients requiring dental procedures, there are no data available to suggest whether discontinuation of bisphosphonate treatment reduces the risk of ONJ. Clinical judgment of the treating physician should guide the management plan of each patient based on individual benefit/risk assessment [see Adverse Reactions (6.2)].

5.5 Musculoskeletal Pain

In postmarketing experience, severe and occasionally incapacitating bone, joint, and/or muscle pain has been reported in patients taking bisphosphonates, including Zoledronic Acid Injection. The time to onset of symptoms varied from one day to several months after starting the drug. Discontinue use if severe symptoms develop. Most patients had relief of symptoms after stopping. A subset had recurrence of symptoms when rechallenged with the same drug or another bisphosphonate [see Adverse Reactions (6.2)].

5.6 Atypical Subtrochanteric and Diaphyseal Femoral Fractures

Atypical subtrochanteric and diaphyseal femoral fractures have been reported in patients receiving bisphosphonate therapy, including Zoledronic Acid Injection. These fractures can occur anywhere in the femoral shaft from just below the lesser trochanter to just above the supracondylar flare and are transverse or short oblique in orientation without evidence of comminution. These fractures occur after minimal or no trauma. Patients may experience thigh or groin pain weeks to months before presenting with a completed femoral fracture. Fractures are often bilateral; therefore the contralateral femur should be examined in bisphosphonate-treated patients who have sustained a femoral shaft fracture. Poor healing of these fractures has also been reported. A number of case reports noted that patients were also receiving treatment with glucocorticoids (such as prednisone or dexamethasone) at the time of fracture. Causality with bisphosphonate therapy has not been established.

Any patient with a history of bisphosphonate exposure who presents with thigh or groin pain in the absence of trauma should be suspected of having an atypical fracture and should be evaluated. Discontinuation of Zoledronic Acid Injection therapy in patients suspected to have an atypical femur fracture should be considered pending evaluation of the patient, based on an individual benefit risk assessment. It is unknown whether the risk of atypical femur fracture continues after stopping therapy.

5.7 Patients with Asthma

While not observed in clinical trials with Zoledronic Acid Injection, there have been reports of bronchoconstriction in aspirin-sensitive patients receiving bisphosphonates.

5.8 Hepatic Impairment

Only limited clinical data are available for use of Zoledronic Acid Injection to treat hypercalcemia of malignancy in patients with hepatic insufficiency, and these data are not adequate to provide guidance on dosage selection or how to safely use Zoledronic Acid Injection in these patients.

5.9 Hypocalcemia

Hypocalcemia has been reported in patients treated with Zoledronic Acid Injection. Cardiac arrhythmias and neurologic adverse events (seizures, tetany, and numbness) have been reported secondary to cases of severe hypocalcemia. In some instances, hypocalcemia may be life-threatening. Caution is advised when Zoledronic Acid Injection is administered with drugs known to cause hypocalcemia, as severe hypocalcemia may develop, [see Drug Interactions (7)]. Serum calcium should be measured and hypocalcemia must be corrected before initiating Zoledronic Acid Injection. Adequately supplement patients with calcium and vitamin D.

5.10 Embryo-Fetal Toxicity

Based on findings from animal studies and its mechanism of action, Zoledronic Acid Injection can cause fetal harm when administered to a pregnant woman. In animal reproduction studies, administration of zoledronic acid to pregnant rats during organogenesis resulted in fetal malformations and embryo-fetal lethality at maternal exposures that were greater than or equal to 2.4 times the human clinical exposure based on area under the curve (AUC). Bisphosphonates, such as Zoledronic Acid Injection, are incorporated into the bone matrix, from where they are gradually released over periods of weeks to years. There may be a risk of fetal harm (e.g., skeletal and other abnormalities) if a woman becomes pregnant after completing a course of bisphosphonate therapy. Advise pregnant women and females of reproductive potential of the potential risk to a fetus. Advise females of reproductive potential to use effective contraception during and after Zoledronic Acid Injection treatment [see Use in Specific Populations (8.1, 8.3), Clinical Pharmacology (12.1)].

6 ADVERSE REACTIONS

6.1 Clinical Trials Experience

Because clinical trials are conducted under widely varying conditions, adverse reaction rates observed in the clinical trials of a drug cannot be directly compared to rates in the clinical trials of another drug and may not reflect the rates observed in practice.

Hypercalcemia of Malignancy

The safety of Zoledronic Acid Injection was studied in 185 patients with hypercalcemia of malignancy (HCM) who received either Zoledronic Acid Injection 4 mg given as a 5-minute intravenous infusion (n = 86) or pamidronate 90 mg given as a 2-hour intravenous infusion (n = 103). The population was aged 33-84 years, 60% male and 81% Caucasian, with breast, lung, head and neck, and renal cancer as the most common forms of malignancy. NOTE: pamidronate 90 mg was given as a 2-hour intravenous infusion. The relative safety of pamidronate 90 mg given as a 2-hour intravenous infusion compared to the same dose given as a 24-hour intravenous infusion has not been adequately studied in controlled clinical trials.

Renal Toxicity

Administration of Zoledronic Acid Injection 4 mg given as a 5-minute intravenous infusion has been shown to result in an increased risk of renal toxicity, as measured by increases in serum creatinine, which can progress to renal failure. The incidence of renal toxicity and renal failure has been shown to be reduced when Zoledronic Acid Injection 4 mg is given as a 15-minute intravenous infusion. Zoledronic Acid Injection should be administered by intravenous infusion over no less than 15 minutes [see Warnings and Precautions (5.3), Dosage and Administration (2.4)].

The most frequently observed adverse reactions were fever, nausea, constipation, anemia, and dyspnea (see Table 4).

Table 4 provides adverse reactions that were reported by 10% or more of the 189 patients treated with Zoledronic Acid Injection 4 mg or pamidronate 90 mg from the two HCM trials. Adverse reactions are listed regardless of presumed causality to study drug.

Table 4: Percentage of Patients with Adverse Reactions Greater Than or Equal to 10% Reported in Hypercalcemia of Malignancy Clinical Trials by Body System
 | Zoledronic Acid Injection 4 mg n (%) |  | Pamidronate 90 mg n (%)
Patients Studied
Total No. of Patients Studied | 86 | (100) | 103 | (100)
Total No. of Patients with any AE | 81 | (94) | 95 | (92)
Body as a Whole
Fever | 38 | (44) | 34 | (33)
Progression of Cancer | 14 | (16) | 21 | (20)
Cardiovascular
Hypotension | 9 | (11) | 2 | (2)
Digestive
Nausea | 25 | (29) | 28 | (27)
Constipation | 23 | (27) | 13 | (13)
Diarrhea | 15 | (17) | 17 | (17)
Abdominal Pain | 14 | (16) | 13 | (13)
Vomiting | 12 | (14) | 17 | (17)
Anorexia | 8 | (9) | 14 | (14)
Hemic and Lymphatic System
Anemia | 19 | (22) | 18 | (18)
Infections
Moniliasis | 10 | (12) | 4 | (4)
Laboratory Abnormalities
Hypophosphatemia | 11 | (13) | 2 | (2)
Hypokalemia | 10 | (12) | 16 | (16)
Hypomagnesemia | 9 | (11) | 5 | (5)
Musculoskeletal
Skeletal Pain | 10 | (12) | 10 | (10)
Nervous
Insomnia | 13 | (15) | 10 | (10)
Anxiety | 12 | (14) | 8 | (8)
Confusion | 11 | (13) | 13 | (13)
Agitation | 11 | (13) | 8 | (8)
Respiratory
Dyspnea | 19 | (22) | 20 | (19)
Coughing | 10 | (12) | 12 | (12)
Urogenital
Urinary Tract Infection | 12 | (14) | 15 | (15)

The following adverse reactions from the two controlled multicenter HCM trials (n = 189) were reported by a greater percentage of patients treated with Zoledronic Acid Injection 4 mg than with pamidronate 90 mg and occurred with a frequency of greater than or equal to 5% but less than 10%. Adverse reactions are listed regardless of presumed causality to study drug: asthenia, chest pain, leg edema, mucositis, dysphagia, granulocytopenia, thrombocytopenia, pancytopenia, nonspecific infection, hypocalcemia, dehydration, arthralgias, headache and somnolence.

Cases of rash, pruritus, and chest pain have been reported following treatment with Zoledronic Acid Injection.

Acute Phase Reaction

Within three days after Zoledronic Acid Injection administration, an acute phase reaction has been reported in patients, with symptoms including pyrexia, fatigue, bone pain and/or arthralgias, myalgias, chills, and influenza-like illness. These symptoms usually resolve within a few days. Pyrexia has been the most commonly associated symptom, occurring in 44% of patients.

Mineral and Electrolyte Abnormalities

Electrolyte abnormalities, most commonly hypocalcemia, hypophosphatemia, and hypomagnesemia, can occur with bisphosphonate use.

Grade 3 and Grade 4 laboratory abnormalities for serum creatinine, serum calcium, serum phosphorus, and serum magnesium observed in two clinical trials of Zoledronic Acid Injection in patients with HCM are shown in Table 5 and 6.

Table 5: Grade 3 Laboratory Abnormalities for Serum Creatinine, Serum Calcium, Serum Phosphorus, and Serum Magnesium in Two Clinical Trials in Patients with HCM
 | Grade 3
Laboratory Parameter | Zoledronic Acid Injection 4 mg |  | Pamidronate 90 mg
 | n/N | (%) | n/N | (%)
Serum Creatinine^1 | 2/86 | (2%) | 3/100 | (3%)
Hypocalcemia^2 | 1/86 | (1%) | 2/100 | (2%)
Hypophosphatemia^3 | 36/70 | (51%) | 27/81 | (33%)
Hypomagnesemia^4 | 0/71 | 0 | 0/84 | 0
^1 Grade 3 (greater than 3x Upper Limit of Normal); Grade 4 (greater than 6x Upper Limit of Normal)
^2 Grade 3 (less than 7 mg/dL); Grade 4 (less than 6 mg/dL)
^3 Grade 3 (less than 2 mg/dL); Grade 4 (less than 1 mg/dL)
^4 Grade 3 (less than 0.8 mEq/L); Grade 4 (less than 0.5 mEq/L)

Table 6: Grade 4 Laboratory Abnormalities for Serum Creatinine, Serum Calcium, Serum Phosphorus, and Serum Magnesium in Two Clinical Trials in Patients with HCM
 | Grade 4
Laboratory Parameter | Zoledronic Acid Injection 4 mg |  | Pamidronate 90 mg
 | n/N | (%) | n/N | (%)
Serum Creatinine^1 | 0/86 | 0 | 1/100 | (1%)
Hypocalcemia^2 | 0/86 | 0 | 0/100 | 0
Hypophosphatemia^3 | 1/70 | (1%) | 4/81 | (5%)
Hypomagnesemia^4 | 0/71 | 0 | 1/84 | (1%)
^1 Grade 3 (greater than 3x Upper Limit of Normal); Grade 4 (greater than 6x Upper Limit of Normal)
^2 Grade 3 (less than 7 mg/dL); Grade 4 (less than 6 mg/dL)
^3 Grade 3 (less than 2 mg/dL); Grade 4 (less than 1 mg/dL)
^4 Grade 3 (less than 0.8 mEq/L); Grade 4 (less than 0.5 mEq/L)

Injection Site Reactions

Local reactions at the infusion site, such as redness or swelling, were observed infrequently. In most cases, no specific treatment is required and the symptoms subside after 24-48 hours.

Ocular Adverse Reactions

Ocular inflammation such as uveitis and scleritis can occur with bisphosphonate use, including Zoledronic Acid Injection. No cases of iritis, scleritis, or uveitis were reported during these clinical trials. However, cases have been seen in postmarketing use [see Adverse Reactions (6.2)].

Multiple Myeloma and Bone Metastases of Solid Tumors

The safety analysis includes patients treated in the core and extension phases of the trials. The analysis includes the 2042 patients treated with Zoledronic Acid Injection 4 mg, pamidronate 90 mg, or placebo in the three controlled multicenter bone metastases trials, including 969 patients completing the efficacy phase of the trial, and 619 patients that continued in the safety extension phase. Only 347 patients completed the extension phases and were followed for 2 years (or 21 months for the other solid tumor patients). The median duration of exposure for safety analysis for Zoledronic Acid Injection 4 mg (core plus extension phases) was 12.8 months for breast cancer and multiple myeloma, 10.8 months for prostate cancer, and 4.0 months for other solid tumors.

Table 7 describes adverse reactions that were reported by 10% or more of patients. Adverse reactions are listed regardless of presumed causality to study drug.

Table 7: Percentage of Patients with Adverse Reactions Greater Than or Equal to 10% Reported in Three Bone Metastases Clinical Trials by Body System
 | Zoledronic Acid Injection 4 mg |  | Pamidronate 90 mg |  | Placebo
 | n (%) |  | n (%) |  | n (%)
Patients Studied
Total No. of Patients | 1031 | (100) | 556 | (100) | 455 | (100)
Total No. of Patients with any AE | 1015 | (98) | 548 | (99) | 445 | (98)
Blood and Lymphatic Anemia Neutropenia Thrombocytopenia | 344 124 102 | (33) (12) (10) | 175 83 53 | (32) (15) (10) | 128 35 20 | (28) (8) (4)
Gastrointestinal
Nausea Vomiting Constipation Diarrhea Abdominal Pain Dyspepsia Stomatitis Sore Throat | 476 333 320 249 143 105 86 82 | (46) (32) (31) (24) (14) (10) (8) (8) | 266 183 162 162 81 74 65 61 | (48) (33) (29) (29) (15) (13) (12) (11) | 171 122 174 83 48 31 14 17 | (38) (27) (38) (18) (11) (7) (3) (4)
General Disorders and Administration Site
Fatigue Pyrexia Weakness Edema Lower Limb Rigors | 398 328 252 215 112 | (39) (32) (24) (21) (11) | 240 172 108 126 62 | (43) (31) (19) (23) (11) | 130 89 114 84 28 | (29) (20) (25) (19) (6)
Infections
Urinary Tract Infection Upper Respiratory Tract Infection | 124 101 | (12) (10) | 50 82 | (9) (15) | 41 30 | (9) (7)
Metabolism
Anorexia Weight Decreased Dehydration Appetite Decreased | 231 164 145 130 | (22) (16) (14) (13) | 81 50 60 48 | (15) (9) (11) (9) | 105 61 59 45 | (23) (13) (13) (10)
Musculoskeletal
Bone Pain | 569 | (55) | 316 | (57) | 284 | (62)
Myalgia | 239 | (23) | 143 | (26) | 74 | (16)
Arthralgia | 216 | (21) | 131 | (24) | 73 | (16)
Back Pain | 156 | (15) | 106 | (19) | 40 | (9)
Pain in Limb | 143 | (14) | 84 | (15) | 52 | (11)
Neoplasms
Malignant Neoplasm Aggravated | 205 | (20) | 97 | (17) | 89 | (20)
Nervous
Headache | 191 | (19) | 149 | (27) | 50 | (11)
Dizziness (excluding vertigo) | 180 | (18) | 91 | (16) | 58 | (13)
Insomnia | 166 | (16) | 111 | (20) | 73 | (16)
Paresthesia | 149 | (15) | 85 | (15) | 35 | (8)
Hypoesthesia | 127 | (12) | 65 | (12) | 43 | (10)
Psychiatric
Depression | 146 | (14) | 95 | (17) | 49 | (11)
Anxiety | 112 | (11) | 73 | (13) | 37 | (8)
Confusion | 74 | (7) | 39 | (7) | 47 | (10)
Respiratory
Dyspnea | 282 | (27) | 155 | (28) | 107 | (24)
Cough | 224 | (22) | 129 | (23) | 65 | (14)
Skin
Alopecia | 125 | (12) | 80 | (14) | 36 | (8)
Dermatitis | 114 | (11) | 74 | (13) | 38 | (8)

Grade 3 and Grade 4 laboratory abnormalities for serum creatinine, serum calcium, serum phosphorus, and serum magnesium observed in three clinical trials of Zoledronic Acid Injection in patients with bone metastases are shown in Tables 8 and 9.

Table 8: Grade 3 Laboratory Abnormalities for Serum Creatinine, Serum Calcium, Serum Phosphorus, and Serum Magnesium in Three Clinical Trials in Patients with Bone Metastases
 | Grade 3
Laboratory Parameter | Zoledronic Acid Injection 4 mg |  | Pamidronate 90 mg |  | Placebo
 | n/N | (%) | n/N | (%) | n/N | (%)
Serum Creatinine^1* | 7/529 | (1%) | 4/268 | (2%) | 4/241 | (2%)
Hypocalcemia^2 | 6/973 | (<1%) | 4/536 | (<1%) | 0/415 | 0
Hypophosphatemia^3 | 115/973 | (12%) | 38/537 | (7%) | 14/415 | (3%)
Hypermagnesemia^4 | 19/971 | (2%) | 2/535 | (<1%) | 8/415 | (2%)
Hypomagnesemia^5 | 1/971 | (<1%) | 0/535 | — | 1/415 | (<1%)
* Serum creatinine data for all patients randomized after the 15-minute infusion amendment
^1 Grade 3 (greater than 3x Upper Limit of Normal); Grade 4 (greater than 6x Upper Limit of Normal)
^2 Grade 3 (less than 7 mg/dL); Grade 4 (less than 6 mg/dL)
^3 Grade 3 (less than 2 mg/dL); Grade 4 (less than 1 mg/dL)
^4 Grade 3 (greater than 3 mEq/L); Grade 4 (greater than 8 mEq/L)
^5 Grade 3 (less than 0.9 mEq/L); Grade 4 (less than 0.7 mEq/L)

Table 9: Grade 4 Laboratory Abnormalities for Serum Creatinine, Serum Calcium, Serum Phosphorus, and Serum Magnesium in Three Clinical Trials in Patients with Bone Metastases
 | Grade 4
Laboratory Parameter | Zoledronic Acid Injection 4 mg |  | Pamidronate 90 mg |  | Placebo
 | n/N | (%) | n/N | (%) | n/N | (%)
Serum Creatinine^1* | 2/529 | (<1%) | 1/268 | (<1%) | 0/241 | 0
Hypocalcemia^2 | 7/973 | (<1%) | 3/536 | (<1%) | 2/415 | (<1%)
Hypophosphatemia^3 | 5/973 | (<1%) | 0/537 | 0 | 1/415 | (<1%)
Hypermagnesemia^4 | 0/971 | 0 | 0/535 | 0 | 2/415 | (<1%)
Hypomagnesemia^5 | 2/971 | (<1%) | 1/535 | (<1%) | 0/415 | 0
* Serum creatinine data for all patients randomized after the 15-minute infusion amendment
^1 Grade 3 (greater than 3x Upper Limit of Normal); Grade 4 (greater than 6x Upper Limit of Normal)
^2 Grade 3 (less than 7 mg/dL); Grade 4 (less than 6 mg/dL)
^3 Grade 3 (less than 2 mg/dL); Grade 4 (less than 1 mg/dL)
^4 Grade 3 (greater than 3 mEq/L); Grade 4 (greater than 8 mEq/L)
^5 Grade 3 (less than 0.9 mEq/L); Grade 4 (less than 0.7 mEq/L)

Among the less frequently occurring adverse reactions (less than 15% of patients), rigors, hypokalemia, influenza-like illness, and hypocalcemia showed a trend for more reactions with bisphosphonate administration (Zoledronic Acid Injection 4 mg and pamidronate groups) compared to the placebo group.

Less common adverse reactions reported more often with Zoledronic Acid Injection 4 mg than pamidronate included decreased weight, which was reported in 16% of patients in the Zoledronic Acid Injection 4 mg group compared with 9% in the pamidronate group. Decreased appetite was reported in slightly more patients in the Zoledronic Acid Injection 4 mg group (13%) compared with the pamidronate (9%) and placebo (10%) groups, but the clinical significance of these small differences is not clear.

Renal Toxicity

In the bone metastases trials, renal deterioration was defined as an increase of 0.5 mg/dL for patients with normal baseline creatinine (less than 1.4 mg/dL) or an increase of 1.0 mg/dL for patients with an abnormal baseline creatinine (greater than or equal to 1.4 mg/dL). The following are data on the incidence of renal deterioration in patients receiving Zoledronic Acid Injection 4 mg over 15 minutes in these trials (see Table 10).

Table 10: Percentage of Patients with Treatment-Emergent Renal Function Deterioration by Baseline Serum Creatinine*
Patient Population/Baseline Creatinine
Multiple Myeloma and Breast Cancer | Zoledronic Acid Injection 4 mg |  | Pamidronate 90 mg
 | n/N | (%) | n/N | (%)
Normal | 27/246 | (11%) | 23/246 | (9%)
Abnormal | 2/26 | (8%) | 2/22 | (9%)
Total | 29/272 | (11%) | 25/268 | (9%)
Solid Tumors | Zoledronic Acid Injection 4 mg |  | Placebo
 | n/N | (%) | n/N | (%)
Normal | 17/154 | (11%) | 10/143 | (7%)
Abnormal | 1/11 | (9%) | 1/20 | (5%)
Total | 18/165 | (11%) | 11/163 | (7%)
Prostate Cancer | Zoledronic Acid Injection 4 mg |  | Placebo
 | n/N | (%) | n/N | (%)
Normal | 12/82 | (15%) | 8/68 | (12%)
Abnormal | 4/10 | (40%) | 2/10 | (20%)
Total | 16/92 | (17%) | 10/78 | (13%)
*Table includes only patients who were randomized to the trial after a protocol amendment that lengthened the infusion duration of Zoledronic Acid Injection to 15 minutes.

The risk of deterioration in renal function appeared to be related to time on study, whether patients were receiving Zoledronic Acid Injection (4 mg over 15 minutes), placebo, or pamidronate.

In the trials and in postmarketing experience, renal deterioration, progression to renal failure, and dialysis have occurred in patients with normal and abnormal baseline renal function, including patients treated with 4 mg infused over a 15-minute period. There have been instances of this occurring after the initial Zoledronic Acid Injection dose.

6.2 Postmarketing Experience

The following adverse reactions have been reported during postapproval use of Zoledronic Acid Injection. Because these reports are from a population of uncertain size and are subject to confounding factors, it is not possible to reliably estimate their frequency or establish a causal relationship to drug exposure.

Osteonecrosis of the Jaw

Cases of osteonecrosis (primarily involving the jaw but also of other anatomical sites including hip, femur and external auditory canal) have been reported predominantly in cancer patients treated with intravenous bisphosphonates including Zoledronic Acid Injection. Many of these patients were also receiving chemotherapy and corticosteroids which may be a risk factor for ONJ. Caution is advised when Zoledronic Acid Injection is administered with anti-angiogenic drugs as an increased incidence of ONJ has been observed with concomitant use of these drugs. Data suggests a greater frequency of reports of ONJ in certain cancers, such as advanced breast cancer and multiple myeloma. The majority of the reported cases are in cancer patients following invasive dental procedures, such as tooth extraction. It is therefore prudent to avoid invasive dental procedures as recovery may be prolonged [see Warnings and Precautions (5.4)].

Acute Phase Reaction

Within three days after Zoledronic Acid Injection administration, an acute phase reaction has been reported, with symptoms including pyrexia, fatigue, bone pain and/or arthralgias, myalgias, chills, influenza-like illness and arthritis with subsequent joint swelling; these symptoms usually resolve within three days of onset, but resolution could take up to 7 to 14 days. However, some of these symptoms have been reported to persist for a longer duration.

Musculoskeletal Pain

Severe and occasionally incapacitating bone, joint, and/or muscle pain has been reported with bisphosphonate use [see Warnings and Precautions (5.5)].

Atypical Subtrochanteric and Diaphyseal Femoral Fractures

Atypical subtrochanteric and diaphyseal femoral fractures have been reported with bisphosphonate therapy, including Zoledronic Acid Injection [see Warnings and Precautions (5.6)].

Ocular Adverse Reactions

Cases of uveitis, scleritis, episcleritis, conjunctivitis, iritis, and orbital inflammation including orbital edema have been reported during postmarketing use. In some cases, symptoms resolved with topical steroids.

Hypersensitivity Reactions

There have been reports of allergic reaction with intravenous zoledronic acid including angioedema and bronchoconstriction. Cases of anaphylactic reaction/shock have been reported. Cases of Stevens-Johnson syndrome and toxic epidermal necrolysis have also been reported.

Additional adverse reactions reported in postmarketing use include:

CNS: taste disturbance, hyperesthesia, tremor; Special Senses: blurred vision; uveitis; Gastrointestinal: dry mouth; Skin: Increased sweating; Musculoskeletal: muscle cramps; Cardiovascular: hypertension, bradycardia, hypotension (associated with syncope or circulatory collapse primarily in patients with underlying risk factors); Respiratory: bronchospasms, interstitial lung disease (ILD) with positive rechallenge; Renal: hematuria, proteinuria, acquired Fanconi syndrome; General Disorders and Administration Site: weight increase, influenza-like illness (pyrexia, asthenia, fatigue or malaise) persisting for greater than 30 days; Laboratory Abnormalities: hyperkalemia, hypernatremia, hypocalcemia (cardiac arrhythmias and neurologic adverse events including seizures, tetany and numbness have been reported due to severe hypocalcemia).

7 DRUG INTERACTIONS

In vitro studies indicate that the plasma protein binding of zoledronic acid is low, with the unbound fraction ranging from 60%-77%. In vitro studies also indicate that zoledronic acid does not inhibit microsomal CYP450 enzymes. In vivo studies showed that zoledronic acid is not metabolized, and is excreted into the urine as the intact drug.

7.1 Aminoglycosides and Calcitonin

Caution is advised when bisphosphonates are administered with aminoglycosides or calcitonin, since these agents may have an additive effect to lower serum calcium level for prolonged periods. This effect has not been reported in Zoledronic Acid Injection clinical trials.

7.2 Loop Diuretics

Caution should also be exercised when Zoledronic Acid Injection is used in combination with loop diuretics due to an increased risk of hypocalcemia.

7.3 Nephrotoxic Drugs

Caution is indicated when Zoledronic Acid Injection is used with other potentially nephrotoxic drugs.

7.4 Thalidomide

No dose adjustment for Zoledronic Acid Injection 4 mg is needed when coadministered with thalidomide. In a pharmacokinetic study of 24 patients with multiple myeloma, Zoledronic Acid Injection 4 mg given as a 15-minute infusion was administered either alone or with thalidomide (100 mg once daily on Days 1-14 and 200 mg once daily on Days 15-28). Coadministration of thalidomide with Zoledronic Acid Injection did not significantly change the pharmacokinetics of zoledronic acid or creatinine clearance.

8 USE IN SPECIFIC POPULATIONS

8.1 Pregnancy

Risk Summary

Based on findings from animal studies and its mechanism of action, Zoledronic Acid Injection can cause fetal harm when administered to a pregnant woman [see Clinical Pharmacology (12.1)]. There are no available data in pregnant women to inform the drug-associated risk. In animal reproduction studies, administration of zoledronic acid to pregnant rats during organogenesis resulted in fetal malformations and embryo-fetal lethality at maternal exposures that were ≥2.4 times the human clinical exposure based on AUC (see Data). Bisphosphonates, such as Zoledronic Acid Injection, are incorporated into the bone matrix, from where they are gradually released over periods of weeks to years. There may be a risk of fetal harm (e.g., skeletal and other abnormalities) if a woman becomes pregnant after completing a course of bisphosphonate therapy. Advise pregnant women and females of reproductive potential of the potential risk to a fetus.

The background risk of major birth defects and miscarriage for the indicated population is unknown; however, in the U.S. general population, the estimated background risk of major birth defects is 2%-4% and of miscarriage is 15%-20% of clinically recognized pregnancies.

Data

Animal Data

In female rats given subcutaneous doses of zoledronic acid of 0.01, 0.03, or 0.1 mg/kg/day beginning 15 days before mating and continuing through gestation, the number of stillbirths was increased and survival of neonates was decreased in the mid- and high-dose groups (greater than or equal to 0.2 times the human systemic exposure following an intravenous dose of 4 mg, based on an AUC comparison). Adverse maternal reactions were observed in all dose groups (with a systemic exposure of greater than or equal to 0.07 times the human systemic exposure following an intravenous dose of 4 mg, based on an AUC comparison) and included dystocia and periparturient mortality in pregnant rats allowed to deliver. Maternal mortality may have been related to drug-induced inhibition of skeletal calcium mobilization, resulting in periparturient hypocalcemia. This appears to be a bisphosphonate-class effect.

In pregnant rats given a subcutaneous dose of zoledronic acid of 0.1, 0.2, or 0.4 mg/kg/day during gestation, adverse fetal reactions were observed in the mid- and high-dose groups (with systemic exposures of 2.4 and 4.8 times, respectively, the human systemic exposure following an intravenous dose of 4 mg, based on an AUC comparison). These adverse reactions included increases in pre- and postimplantation losses, decreases in viable fetuses, and fetal skeletal, visceral, and external malformations. Fetal skeletal effects observed in the high-dose group included unossified or incompletely ossified bones, thickened, curved, or shortened bones, wavy ribs, and shortened jaw. Other adverse fetal reactions observed in the high-dose group included reduced lens, rudimentary cerebellum, reduction or absence of liver lobes, reduction of lung lobes, vessel dilation, cleft palate, and edema. Skeletal variations were also observed in the low-dose group at 0.1 mg/kg/day (with systemic exposure of 1.2 times the human systemic exposure following an intravenous dose of 4 mg, based on an AUC comparison). Signs of maternal toxicity were observed in the high-dose group and included reduced body weights and food consumption, indicating that maximal exposure levels were achieved in this study.

In pregnant rabbits given subcutaneous doses of zoledronic acid of 0.01, 0.03, or 0.1 mg/kg/day during gestation (less than or equal to 0.5 times the human intravenous dose of 4 mg, based on a comparison of relative body surface areas), no adverse fetal reactions were observed. Maternal mortality and abortion occurred in all treatment groups (at doses greater than or equal to 0.05 times the human intravenous dose of 4 mg, based on a comparison of relative body surface areas). Adverse maternal reactions were associated with, and may have been caused by, drug-induced hypocalcemia.

8.2 Lactation

Risk Summary

After administration of Zoledronic Acid Injection, it is not known whether zoledronic acid is present in human milk, or whether it affects milk production or the breastfed child. Zoledronic acid binds to bone long term and may be released over periods of weeks to years. Because of the potential for serious adverse reactions in a breastfed child, advise a lactating woman not to breastfeed during and after Zoledronic Acid Injection treatment.

8.3 Females and Males of Reproductive Potential

Pregnancy Testing

Verify pregnancy status of females of reproductive potential prior to initiation of Zoledronic Acid Injection.

Contraception

Females

Zoledronic Acid Injection can cause fetal harm when administered to a pregnant woman [see Use in Specific Populations (8.1)]. Zoledronic acid binds to bone long term and may be released over periods of weeks to years. Advise females of reproductive potential to use effective contraception during and after Zoledronic Acid Injection treatment.

Infertility

Females

Based on animal studies, zoledronic acid injection may impair fertility in females of reproductive potential [see Nonclinical Toxicology (13.1)].

8.4 Pediatric Use

Zoledronic Acid Injection is not indicated for use in children.

The safety and effectiveness of zoledronic acid was studied in a one-year, active-controlled trial of 152 pediatric subjects (74 receiving zoledronic acid). The enrolled population was subjects with severe osteogenesis imperfecta, aged 1-17 years, 55% male, 84% Caucasian, with a mean lumbar spine bone mineral density (BMD) of 0.431 gm/cm^2, which is 2.7 standard deviations below the mean for age-matched controls (BMD Z-score of -2.7). At one year, increases in BMD were observed in the zoledronic acid treatment group. However, changes in BMD in individual patients with severe osteogenesis imperfecta did not necessarily correlate with the risk for fracture or the incidence or severity of chronic bone pain. The adverse reactions observed with Zoledronic Acid Injection use in children did not raise any new safety findings beyond those previously seen in adults treated for hypercalcemia of malignancy or bone metastases. However, adverse reactions seen more commonly in pediatric patients included pyrexia (61%), arthralgia (26%), hypocalcemia (22%) and headache (22%). These reactions, excluding arthralgia, occurred most frequently within 3 days after the first infusion and became less common with repeat dosing. Because of long-term retention in bone, Zoledronic Acid Injection should only be used in children if the potential benefit outweighs the potential risk.

Plasma zoledronic acid concentration data was obtained from 10 patients with severe osteogenesis imperfecta (4 in the age group of 3-8 years and 6 in the age group of 9-17 years) infused with 0.05 mg/kg dose over 30 min. Mean Cmax and AUC(0-last) was 167 ng/mL and 220 ng∙h/mL, respectively. The plasma concentration time profile of zoledronic acid in pediatric patients represent a multi-exponential decline, as observed in adult cancer patients at an approximately equivalent mg/kg dose.

8.5 Geriatric Use

Clinical studies of Zoledronic Acid Injection in hypercalcemia of malignancy included 34 patients who were 65 years of age or older. No significant differences in response rate or adverse reactions were seen in geriatric patients receiving Zoledronic Acid Injection as compared to younger patients. Controlled clinical studies of Zoledronic Acid Injection in the treatment of multiple myeloma and bone metastases of solid tumors in patients over age 65 revealed similar efficacy and safety in older and younger patients. Because decreased renal function occurs more commonly in the elderly, special care should be taken to monitor renal function.

10 OVERDOSAGE

Clinical experience with acute overdosage of Zoledronic Acid Injection is limited. Two patients received Zoledronic Acid Injection 32 mg over 5 minutes in clinical trials. Neither patient experienced any clinical or laboratory toxicity. Overdosage may cause clinically significant hypocalcemia, hypophosphatemia, and hypomagnesemia. Clinically relevant reductions in serum levels of calcium, phosphorus, and magnesium should be corrected by intravenous administration of calcium gluconate, potassium or sodium phosphate, and magnesium sulfate, respectively.

In an open-label study of zoledronic acid 4 mg in breast cancer patients, a female patient received a single 48-mg dose of zoledronic acid in error. Two days after the overdose, the patient experienced a single episode of hyperthermia (38°C), which resolved after treatment. All other evaluations were normal, and the patient was discharged seven days after the overdose.

A patient with non-Hodgkin's lymphoma received zoledronic acid 4 mg daily on four successive days for a total dose of 16 mg. The patient developed paresthesia and abnormal liver function tests with increased GGT (nearly 100 unit/L, each value unknown). The outcome of this case is not known.

In controlled clinical trials, administration of Zoledronic Acid Injection 4 mg as an intravenous infusion over 5 minutes has been shown to increase the risk of renal toxicity compared to the same dose administered as a 15-minute intravenous infusion. In controlled clinical trials, Zoledronic Acid Injection 8 mg has been shown to be associated with an increased risk of renal toxicity compared to Zoledronic Acid Injection 4 mg, even when given as a 15-minute intravenous infusion, and was not associated with added benefit in patients with hypercalcemia of malignancy [see Dosage and Administration (2.4)].

11 DESCRIPTION

Zoledronic Acid Injection contains zoledronic acid, a bisphosphonic acid which is an inhibitor of osteoclastic bone resorption. Zoledronic acid monohydrate is designated chemically as (1-Hydroxy-2-imidazol-1-yl-phosphonoethyl) phosphonic acid monohydrate and its structural formula is as following:

Zoledronic acid monohydrate is a white crystalline powder. Its molecular formula is C5H10N2O7P2•H2O and its molar mass is 290.1g/mol. Zoledronic acid monohydrate is highly soluble in 0.1N sodium hydroxide solution, sparingly soluble in water and 0.1N hydrochloric acid, and practically insoluble in organic solvents. The pH of a 0.7% solution of zoledronic acid in water is approximately 2.0.

Zoledronic Acid Injection is available in bags as a sterile liquid solution for intravenous infusion. Each 100 mL bag contains 4.264 mg of zoledronic acid monohydrate (equivalent to 4 mg zoledronic acid on an anhydrous basis), 900 mg of sodium chloride, USP, 220 mg of mannitol, USP, water for injection q.s. and 24 mg of sodium citrate to adjust pH. The pH of the solution is approximately 5.5 to 6.5.

12 CLINICAL PHARMACOLOGY

12.1 Mechanism of Action

The principal pharmacologic action of zoledronic acid is inhibition of bone resorption. Although the antiresorptive mechanism is not completely understood, several factors are thought to contribute to this action. In vitro, zoledronic acid inhibits osteoclastic activity and induces osteoclast apoptosis. Zoledronic acid also blocks the osteoclastic resorption of mineralized bone and cartilage through its binding to bone. Zoledronic acid inhibits the increased osteoclastic activity and skeletal calcium release induced by various stimulatory factors released by tumors.

12.2 Pharmacodynamics

Clinical studies in patients with hypercalcemia of malignancy (HCM) showed that single-dose infusions of Zoledronic Acid Injection are associated with decreases in serum calcium and phosphorus and increases in urinary calcium and phosphorus excretion.

Osteoclastic hyperactivity resulting in excessive bone resorption is the underlying pathophysiologic derangement in hypercalcemia of malignancy (HCM, tumor-induced hypercalcemia) and metastatic bone disease. Excessive release of calcium into the blood as bone is resorbed results in polyuria and gastrointestinal disturbances, with progressive dehydration and decreasing glomerular filtration rate. This, in turn, results in increased renal resorption of calcium, setting up a cycle of worsening systemic hypercalcemia. Reducing excessive bone resorption and maintaining adequate fluid administration are, therefore, essential to the management of hypercalcemia of malignancy.

Patients who have hypercalcemia of malignancy can generally be divided into two groups according to the pathophysiologic mechanism involved: humoral hypercalcemia and hypercalcemia due to tumor invasion of bone. In humoral hypercalcemia, osteoclasts are activated and bone resorption is stimulated by factors such as parathyroid hormone-related protein, which are elaborated by the tumor and circulate systemically. Humoral hypercalcemia usually occurs in squamous cell malignancies of the lung or head and neck or in genitourinary tumors such as renal cell carcinoma or ovarian cancer. Skeletal metastases may be absent or minimal in these patients.

Extensive invasion of bone by tumor cells can also result in hypercalcemia due to local tumor products that stimulate bone resorption by osteoclasts. Tumors commonly associated with locally mediated hypercalcemia include breast cancer and multiple myeloma.

Total serum calcium levels in patients who have hypercalcemia of malignancy may not reflect the severity of hypercalcemia, since concomitant hypoalbuminemia is commonly present. Ideally, ionized calcium levels should be used to diagnose and follow hypercalcemic conditions; however, these are not commonly or rapidly available in many clinical situations. Therefore, adjustment of the total serum calcium value for differences in albumin levels (corrected serum calcium, CSC) is often used in place of measurement of ionized calcium; several nomograms are in use for this type of calculation [see Dosage and Administration (2.1)].

12.3 Pharmacokinetics

Pharmacokinetic data in patients with hypercalcemia are not available.

Distribution

Single or multiple (every 28 days) 5-minute or 15-minute infusions of 2, 4, 8, or 16 mg Zoledronic Acid Injection were given to 64 patients with cancer and bone metastases. The post-infusion decline of zoledronic acid concentrations in plasma was consistent with a triphasic process showing a rapid decrease from peak concentrations at end of infusion to less than 1% of Cmax 24 hours post-infusion with population half-lives of t1/2α 0.24 hours and t1/2β 1.87 hours for the early disposition phases of the drug. The terminal elimination phase of zoledronic acid was prolonged, with very low concentrations in plasma between Days 2 and 28 post-infusion, and a terminal elimination half-life t1/2γ of 146 hours. The area under the plasma concentration versus time curve (AUC0-24h) of zoledronic acid was dose proportional from 2-16 mg. The accumulation of zoledronic acid measured over three cycles was low, with mean AUC0-24h ratios for cycles 2 and 3 versus 1 of 1.13 ± 0.30 and 1.16 ± 0.36, respectively.

In vitro and ex vivo studies showed low affinity of zoledronic acid for the cellular components of human blood, with a mean blood to plasma concentration ratio of 0.59 in a concentration range of 30 ng/mL to 5000 ng/mL. In vitro, the plasma protein binding is low, with the unbound fraction ranging from 60% at 2 ng/mL to 77% at 2000 ng/mL of zoledronic acid.

Metabolism

Zoledronic acid does not inhibit human P450 enzymes in vitro. Zoledronic acid does not undergo biotransformation in vivo. In animal studies, less than 3% of the administered intravenous dose was found in the feces, with the balance either recovered in the urine or taken up by bone, indicating that the drug is eliminated intact via the kidney. Following an intravenous dose of 20 nCi ^14C-zoledronic acid in a patient with cancer and bone metastases, only a single radioactive species with chromatographic properties identical to those of parent drug was recovered in urine, which suggests that zoledronic acid is not metabolized.

Excretion

In 64 patients with cancer and bone metastases, on average (± SD) 39 ± 16% of the administered zoledronic acid dose was recovered in the urine within 24 hours, with only trace amounts of drug found in urine post-Day 2. The cumulative percent of drug excreted in the urine over 0-24 hours was independent of dose. The balance of drug not recovered in urine over 0-24 hours, representing drug presumably bound to bone, is slowly released back into the systemic circulation, giving rise to the observed prolonged low plasma concentrations. The 0-24 hour renal clearance of zoledronic acid was 3.7 ± 2.0 L/h.

Zoledronic acid clearance was independent of dose but dependent upon the patient's creatinine clearance. In a study in patients with cancer and bone metastases, increasing the infusion time of a 4-mg dose of zoledronic acid from 5 minutes (n = 5) to 15 minutes (n = 7) resulted in a 34% decrease in the zoledronic acid concentration at the end of the infusion ([mean ± SD] 403 ± 118 ng/mL versus 264 ± 86 ng/mL) and a 10% increase in the total AUC (378 ± 116 ng x h/mL versus 420 ± 218 ng x h/mL). The difference between the AUC means was not statistically significant.

Special Populations

Pediatrics

Zoledronic Acid Injection is not indicated for use in children [see Use in Specific Populations (8.4)].

Geriatrics

The pharmacokinetics of zoledronic acid were not affected by age in patients with cancer and bone metastases who ranged in age from 38 years to 84 years.

Race

Population pharmacokinetic analyses did not indicate any differences in pharmacokinetics among Japanese and North American (Caucasian and African American) patients with cancer and bone metastases.

Hepatic Insufficiency

No clinical studies were conducted to evaluate the effect of hepatic impairment on the pharmacokinetics of zoledronic acid.

Renal Insufficiency

The pharmacokinetic studies conducted in 64 cancer patients represented typical clinical populations with normal to moderately impaired renal function. Compared to patients with normal renal function (N = 37), patients with mild renal impairment (N = 15) showed an average increase in plasma AUC of 15%, whereas patients with moderate renal impairment (N = 11) showed an average increase in plasma AUC of 43%. Limited pharmacokinetic data are available for Zoledronic Acid Injection in patients with severe renal impairment (creatinine clearance less than 30 mL/min). Based on population PK/PD modeling, the risk of renal deterioration appears to increase with AUC, which is doubled at a creatinine clearance of 10 mL/min. Creatinine clearance is calculated by the Cockcroft-Gault formula:

CrCl = [140-age (years)] x weight (kg) {x 0.85 for female patients}
  [72 x serum creatinine (mg/dL)]

Zoledronic Acid Injection systemic clearance in individual patients can be calculated from the population clearance of Zoledronic Acid Injection, CL (L/h)=6.5(CrCl/90)^0.4. These formulae can be used to predict the Zoledronic Acid Injection AUC in patients, where CL = Dose/AUC0-∞. The average AUC0-24 in patients with normal renal function was 0.42 mg•h/L and the calculated AUC0-∞ for a patient with creatinine clearance of 75 mL/min was 0.66 mg•h/L following a 4-mg dose of Zoledronic Acid Injection. However, efficacy and safety of adjusted dosing based on these formulae have not been prospectively assessed [see Warnings and Precautions (5.3)].

13 NONCLINICAL TOXICOLOGY

13.1 Carcinogenesis, Mutagenesis, Impairment of Fertility

Standard lifetime carcinogenicity bioassays were conducted in mice and rats. Mice were given oral doses of zoledronic acid of 0.1, 0.5, or 2.0 mg/kg/day. There was an increased incidence of Harderian gland adenomas in males and females in all treatment groups (at doses greater than or equal to 0.002 times a human intravenous dose of 4 mg, based on a comparison of relative body surface areas). Rats were given oral doses of zoledronic acid of 0.1, 0.5, or 2.0 mg/kg/day. No increased incidence of tumors was observed (at doses less than or equal to 0.2 times the human intravenous dose of 4 mg, based on a comparison of relative body surface areas).

Zoledronic acid was not genotoxic in the Ames bacterial mutagenicity assay, in the Chinese hamster ovary cell assay, or in the Chinese hamster gene mutation assay, with or without metabolic activation. Zoledronic acid was not genotoxic in the in vivo rat micronucleus assay.

Female rats were given subcutaneous doses of zoledronic acid of 0.01, 0.03, or 0.1 mg/kg/day beginning 15 days before mating and continuing through gestation. Effects observed in the high-dose group (with systemic exposure of 1.2 times the human systemic exposure following an intravenous dose of 4 mg, based on AUC comparison) included inhibition of ovulation and a decrease in the number of pregnant rats. Effects observed in both the mid-dose group (with systemic exposure of 0.2 times the human systemic exposure following an intravenous dose of 4 mg, based on an AUC comparison) and high-dose group included an increase in preimplantation losses and a decrease in the number of implantations and live fetuses.

14 CLINICAL STUDIES

14.1 Hypercalcemia of Malignancy

Two identical multicenter, randomized, double-blind, double-dummy studies of Zoledronic Acid Injection 4 mg given as a 5-minute intravenous infusion or pamidronate 90 mg given as a 2-hour intravenous infusion were conducted in 185 patients with hypercalcemia of malignancy (HCM). NOTE: Administration of Zoledronic Acid Injection 4 mg given as a 5-minute intravenous infusion has been shown to result in an increased risk of renal toxicity, as measured by increases in serum creatinine, which can progress to renal failure. The incidence of renal toxicity and renal failure has been shown to be reduced when Zoledronic Acid Injection 4 mg is given as a 15-minute intravenous infusion. Zoledronic Acid Injection should be administered by intravenous infusion over no less than 15 minutes [see Warnings and Precautions (5.1, 5.2), Dosage and Administration (2.4)]. The treatment groups in the clinical studies were generally well balanced with regards to age, sex, race, and tumor types. The mean age of the study population was 59 years; 81% were Caucasian, 15% were Black, and 4% were of other races. Sixty percent (60%) of the patients were male. The most common tumor types were lung, breast, head and neck, and renal.

In these studies, HCM was defined as a corrected serum calcium (CSC) concentration of greater than or equal to 12.0 mg/dL (3.00 mmol/L). The primary efficacy variable was the proportion of patients having a complete response, defined as the lowering of the CSC to less than or equal to 10.8 mg/dL (2.70 mmol/L) within 10 days after drug infusion.

To assess the effects of Zoledronic Acid Injection versus those of pamidronate, the two multicenter HCM studies were combined in a preplanned analysis. The results of the primary analysis revealed that the proportion of patients that had normalization of corrected serum calcium by Day 10 were 88% and 70% for Zoledronic Acid Injection 4 mg and pamidronate 90 mg, respectively (P = 0.002) (see Figure 1). In these studies, no additional benefit was seen for Zoledronic Acid Injection 8 mg over Zoledronic Acid Injection 4 mg; however, the risk of renal toxicity of Zoledronic Acid Injection 8 mg was significantly greater than that seen with Zoledronic Acid Injection 4 mg.

Figure 1: Proportion of Complete Responders by Day 10 in Pooled HCM Studies

Secondary efficacy variables from the pooled HCM studies included the proportion of patients who had normalization of corrected serum calcium (CSC) by Day 4; the proportion of patients who had normalization of CSC by Day 7; time to relapse of HCM; and duration of complete response. Time to relapse of HCM was defined as the duration (in days) of normalization of serum calcium from study drug infusion until the last CSC value less than 11.6 mg/dL (less than 2.90 mmol/L). Patients who did not have a complete response were assigned a time to relapse of 0 days. Duration of complete response was defined as the duration (in days) from the occurrence of a complete response until the last CSC less than or equal to 10.8 mg/dL (2.70 mmol/L). The results of these secondary analyses for Zoledronic Acid Injection 4 mg and pamidronate 90 mg are shown in Table 11.

Table 11: Secondary Efficacy Variables in Pooled HCM Studies
 |  | Zoledronic Acid Injection 4 mg |  | Pamidronate 90 mg
Complete Response | N | Response Rate | N | Response Rate
By Day 4 | 86 | 45.3% | 99 | 33.3%
By Day 7 | 86 | 82.6%* | 99 | 63.6%
Duration of Response | N | Median Duration (Days) | N | Median Duration (Days)
Time to Relapse | 86 | 30* | 99 | 17
Duration of Complete Response | 76 | 32 | 69 | 18
*P less than 0.05 versus pamidronate 90 mg.

14.2 Clinical Trials in Multiple Myeloma and Bone Metastases of Solid Tumors

Table 12 describes an overview of the efficacy population in three randomized Zoledronic Acid Injection trials in patients with multiple myeloma and bone metastases of solid tumors. These trials included a pamidronate-controlled study in breast cancer and multiple myeloma, a placebo-controlled study in prostate cancer, and a placebo-controlled study in other solid tumors. The prostate cancer study required documentation of previous bone metastases and 3 consecutive rising PSAs while on hormonal therapy. The other placebo-controlled solid tumor study included patients with bone metastases from malignancies other than breast cancer and prostate cancer, including NSCLC, renal cell cancer, small cell lung cancer, colorectal cancer, bladder cancer, GI/genitourinary cancer, head and neck cancer, and others. These trials were comprised of a core phase and an extension phase. In the solid tumor, breast cancer and multiple myeloma trials, only the core phase was evaluated for efficacy as a high percentage of patients did not choose to participate in the extension phase. In the prostate cancer trials, both the core and extension phases were evaluated for efficacy showing the Zoledronic Acid Injection effect during the first 15 months was maintained without decrement or improvement for another 9 months. The design of these clinical trials does not permit assessment of whether more than one-year administration of Zoledronic Acid Injection is beneficial. The optimal duration of Zoledronic Acid Injection administration is not known.

The studies were amended twice because of renal toxicity. The Zoledronic Acid Injection infusion duration was increased from 5 minutes to 15 minutes. After all patients had been accrued, but while dosing and follow-up continued, patients in the 8 mg Zoledronic Acid Injection treatment arm were switched to 4 mg due to toxicity. Patients who were randomized to the Zoledronic Acid Injection 8 mg group are not included in these analyses.

Table 12: Overview of Efficacy Population for Phase III Studies
Patient Population | No. of Patients | Zoledronic Acid Injection Dose | Control | Median Duration (Planned Duration) Zoledronic Acid Injection 4 mg
Multiple myeloma or metastatic breast cancer | 1,648 | 4 and 8* mg Q3-4 weeks | Pamidronate 90 mg Q3-4 weeks | 12.0 months (13 months)
Metastatic prostate cancer | 643 | 4 and 8* mg Q3 weeks | Placebo | 10.5 months (15 months)
Metastatic solid tumor other than breast or prostate cancer | 773 | 4 and 8* mg Q3 weeks | Placebo | 3.8 months (9 months)
*Patients who were randomized to the 8 mg Zoledronic Acid Injection group are not included in any of the analyses in this package insert.

Each study evaluated skeletal-related events (SREs), defined as any of the following: pathologic fracture, radiation therapy to bone, surgery to bone, or spinal cord compression. Change in antineoplastic therapy due to increased pain was a SRE in the prostate cancer study only. Planned analyses included the proportion of patients with a SRE during the study and time to the first SRE. Results for the two Zoledronic Acid Injection placebo-controlled studies are given in Table 13.

Table 13: Zoledronic Acid Injection Compared to Placebo in Patients with Bone Metastases from Prostate Cancer or Other Solid Tumors
I. Analysis of Proportion of Patients with a SRE^1 |  |  |  |  | II. Analysis of Time to the First SRE
Study | Study Arm & Patient Number | Proportion | Difference^2 & 95% CI | P-value | Median (Days) | Hazard Ratio^3 & 95% CI | P-value
Prostate Cancer | Zoledronic Acid Injection 4 mg (n = 214) | 33% | -11% (-20%, -1%) | 0.02 | Not Reached | 0.67 (0.49, 0.91) | 0.011
 | Placebo (n = 208) | 44% |  |  | 321
Solid Tumors | Zoledronic Acid Injection 4 mg (n = 257) | 38% | -7% (-15%, 2%) | 0.13 | 230 | 0.73 (0.55, 0.96) | 0.023
 | Placebo (n = 250) | 44% |  |  | 163
^1SRE = Skeletal-Related Event
^2Difference for the proportion of patients with a SRE of Zoledronic Acid Injection 4 mg versus placebo.
^3Hazard ratio for the first occurrence of a SRE of Zoledronic Acid Injection 4 mg versus placebo.

In the breast cancer and myeloma trial, efficacy was determined by a noninferiority analysis comparing Zoledronic Acid Injection to pamidronate 90 mg for the proportion of patients with a SRE. This analysis required an estimation of pamidronate efficacy. Historical data from 1,128 patients in three pamidronate placebo-controlled trials demonstrated that pamidronate decreased the proportion of patients with a SRE by 13.1% (95% CI = 7.3%, 18.9%). Results of the comparison of treatment with Zoledronic Acid Injection compared to pamidronate are given in Table 14.

Table 14: Zoledronic Acid Injection Compared to Pamidronate in Patients with Multiple Myeloma or Bone Metastases from Breast Cancer
I. Analysis of Proportion of Patients with a SRE^1 |  |  |  |  | II. Analysis of Time to the First SRE
Study | Study Arm & Patient Number | Proportion | Difference^2 & 95% CI | P-value | Median (Days) | Hazard Ratio^3 & 95% CI | P-value
Multiple Myeloma & Breast Cancer | Zoledronic Acid Injection 4 mg (n = 561) | 44% | -2% (-7.9%, 3.7%) | 0.46 | 373 | 0.92 (0.77, 1.09) |  | 0.32
 | Pamidronate (n = 555) | 46% |  |  | 363
^1SRE=Skeletal-Related Event.
^2Difference for the proportion of patients with a SRE of Zoledronic Acid Injection 4 mg versus pamidronate 90 mg.
^3Hazard ratio for the first occurrence of a SRE of Zoledronic Acid Injection 4 mg versus pamidronate 90 mg.

16 HOW SUPPLIED/STORAGE AND HANDLING

Zoledronic Acid Injection is supplied as follows:

NDC | Zoledronic Acid Injection (0.04 mg per mL) | Package Factor
25021-826-82 | 4 mg per 100 mL in a Single-Dose Bag | 1 bag per carton
25021-826-87 | 4 mg per 100 mL in a Single-Dose Bag | 5 bags per carton

Storage Conditions

Store at 20°C to 25°C (68°F to 77°F); excursions permitted to 15°C to 30°C (59°F to 86°F). [See USP Controlled Room Temperature.]

Discard unused portion.

Sterile, Nonpyrogenic, Preservative-free, DEHP-free, PVC-free.
The container and container closure are not made with natural rubber latex.

17 PATIENT COUNSELING INFORMATION

Drugs with Same Active Ingredient or in the Same Drug Class

Inform patients not to take Reclast or other bisphosphonates during the course of their Zoledronic Acid Injection therapy [see Warnings and Precautions (5.1)].

Renal Impairment

- Instruct patients to tell their doctor if they have kidney problems before being given Zoledronic Acid Injection.
- Inform patients of the importance of getting their blood tests (serum creatinine) during the course of their Zoledronic Acid Injection therapy [see Warnings and Precautions (5.3)].

Osteonecrosis of the Jaw (ONJ)

- Advise patients to have a dental examination prior to treatment with Zoledronic Acid Injection and to avoid invasive dental procedures during treatment.
- Inform patients of the importance of good dental hygiene, routine dental care, and regular dental check-ups.
- Advise patients to immediately tell their doctor about any oral symptoms such as loosening of a tooth, pain, swelling, or non-healing of sores or discharge during treatment with Zoledronic Acid Injection [see Warnings and Precautions (5.4)].

Musculoskeletal Pain

Advise patients to immediately tell their doctor about any severe bone, joint, and/or muscle pain [see Warnings and Precautions (5.5)].

Atypical Subtrochanteric and Diaphyseal Femoral Fracture

Advise patients to report any thigh, hip, or groin pain. It is unknown whether the risk of atypical femur fracture continues after stopping therapy [see Warnings and Precautions (5.6)].

Patients with Asthma

There have been reports of bronchoconstriction in aspirin-sensitive patients receiving bisphosphonates, including zoledronic acid. Before being given zoledronic acid, instruct patients to tell their doctor if they are aspirin-sensitive [see Warnings and Precautions (5.7)].

Hypocalcemia

Advise patients with multiple myeloma and bone metastasis of solid tumors to take an oral calcium supplement of 500 mg and a multiple vitamin containing 400 international units of vitamin D daily [see Warnings and Precautions (5.9)].

Embryo-Fetal Toxicity

- Zoledronic Acid Injection should not be given if the patient is pregnant or plans to become pregnant. Inform female patients of the risk to a fetus and potential loss of the pregnancy [see Warnings and Precautions (5.10)].
- Advise females of reproductive potential to use effective contraception during and after treatment with Zoledronic Acid Injection [see Warnings and Precautions (5.10), Use in Specific Populations (8.1, 8.3)].

Lactation

Advise lactating women not to breastfeed during and after treatment with Zoledronic Acid Injection [see Use in Specific Populations (8.2)].

Common Adverse Reactions

- Advise patients that the most common side effects of Zoledronic Acid Injection are nausea, fatigue, anemia, bone pain, constipation, fever, vomiting, and dyspnea.

Brands listed are the trademarks of their respective owners.

sagent®
Mfd. for SAGENT Pharmaceuticals
Schaumburg, IL 60173 (USA)
Made in Switzerland
©2025 Sagent Pharmaceuticals

Revised: January 2025

PACKAGE LABEL – PRINCIPAL DISPLAY PANEL – Bag Label

NDC 25021-826-82

100 mL

Rx only

Zoledronic Acid Injection

4 mg per 100 mL

(0.04 mg per mL)

For Intravenous Infusion